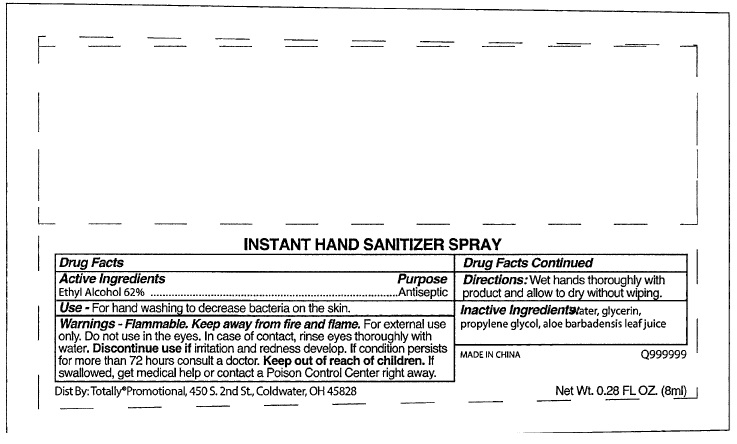 DRUG LABEL: Hand Sanitizer
NDC: 71087-004 | Form: LIQUID
Manufacturer: CASAD Company, Inc
Category: otc | Type: HUMAN OTC DRUG LABEL
Date: 20241009

ACTIVE INGREDIENTS: ALCOHOL 62 mL/100 mL
INACTIVE INGREDIENTS: WATER; GLYCERIN; PROPYLENE GLYCOL; ALOE VERA LEAF

INSTANT HAND SANITIZER SPRAY

Drug Facts Active Ingredient

Ethyl Alcohol 62%

Purpose

Antiseptic

Use

For hand washing to decrease bacteria on the skin. Recommended for repeated use.

Warnings

Flammable. Keep away from fire and flame. For external use

only. Do not use in the eyes. In case of contact, rinse eyes thoroughly with
water. Discontinue use if irritation and redness develop. If condition persists
for more than 72 hours consult a doctor.

Keep out of reach of children. If swallowed, get medical help or
contact a Poison Control Center right away.

Directions

Wet hands thoroughly with product and allow to dry without wiping.

Inactive Ingredients

Water, glycerin, propylene glycol, aloe barbadensis leaf juice

INSTANT HAND SANITIZER SPRAY product label

INSTANT HAND SANITIZER SPRAY

Made in China

Dist By:Totally®Promotional, 450 S. 2nd St., Coldwater, OH 45828

res